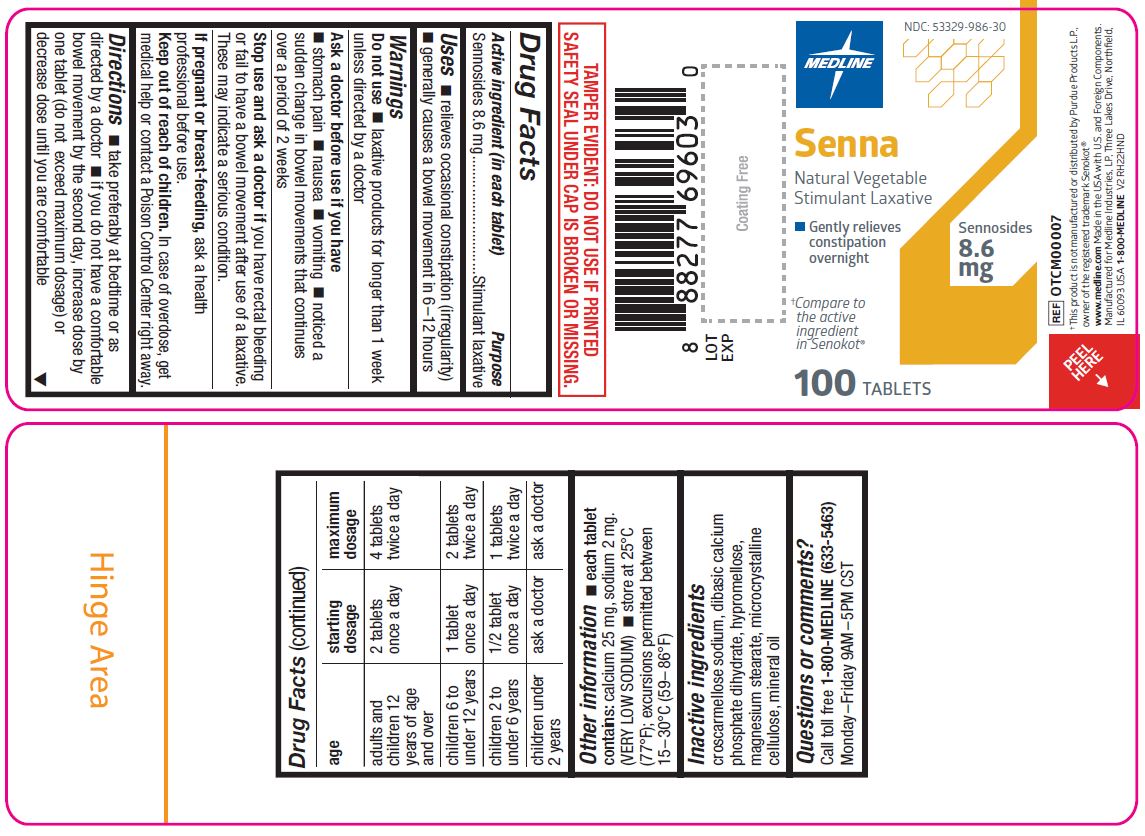 DRUG LABEL: Senna Natural Vegetable
NDC: 53329-986 | Form: TABLET, COATED
Manufacturer: Medline Industries, LP
Category: otc | Type: HUMAN OTC DRUG LABEL
Date: 20241212

ACTIVE INGREDIENTS: SENNOSIDES A AND B 8.6 mg/1 1
INACTIVE INGREDIENTS: CROSCARMELLOSE SODIUM; DIBASIC CALCIUM PHOSPHATE DIHYDRATE; HYPROMELLOSE, UNSPECIFIED; MAGNESIUM STEARATE; MICROCRYSTALLINE CELLULOSE; MINERAL OIL

986 Senna

Active ingredient (in each tablet)

Sennosides 8.6 mg

Purpose

Stimulant laxative

Uses

- relieves occational constipation (irregularity)
- generally causes bowel movement in 6-12 hours

Warnings

Do not use

- laxative products for longer than 1 week unless directed by a doctor

Ask a doctor before use if you have

- stomach pain
- nausea
- vomiting
- noticed a sudden change in bowel movements that continues over a period of 2 weeks

Stop use and ask a doctor if

you have rectal bleeding or fail to have a bowel movement after use of a laxative. These may indicate a serious condition.

If pregnant or breast-feeding,

ask a health professional before use.

Keep out of reach of children.

In case of overdose, get medical help or contact a Poison Control Center right away.

Directions

- take preferably at bedtime or as directed by a doctor
- if you do not have a comfortable bowel movement by the second day, increase dose by one tablet (do not exceed maximum dosage) or decrease dose until you are comfortable

age | starting dosage | maximum dosage
adults and children 12 years age and over | 2 tablets once a day | 4 tablets twice a day
children 6 to under 12 years | 1 tablet once a day | 2 tablets twice a day
children 2 to under 6 years | 1/2 tablet once a day | 1 tablet twice a day
children under 2 years | ask a doctor | ask a doctor

Other information

- each tablet contains: calcium 25 mg, sodium 2 mg. (VERY LOW SODIUM)
- store at 25°C (77°F), excursions permitted between 15°-30°C (59°-86°F)

Inactive ingredients

croscarmellose sodium, dibasic calcium phosphate dihydrate, hypromellose, magnesium stearate, microcrystalline cellulose, mineral oil

Questions or comments?

Call toll free 1-800-MEDLINE (633-5463)
Monday-Friday 9AM-5PM CST

Manufacturing Information

Manufactured by:

Medline Industries, LP

Three Lakes Drive, Northfield, IL 60093 USA

Made in the USA with U.S. and Foreign Components

www.medline.com

1-800-MEDLINE (633-5463)

REF: OTCM00007

V2 RH22HND